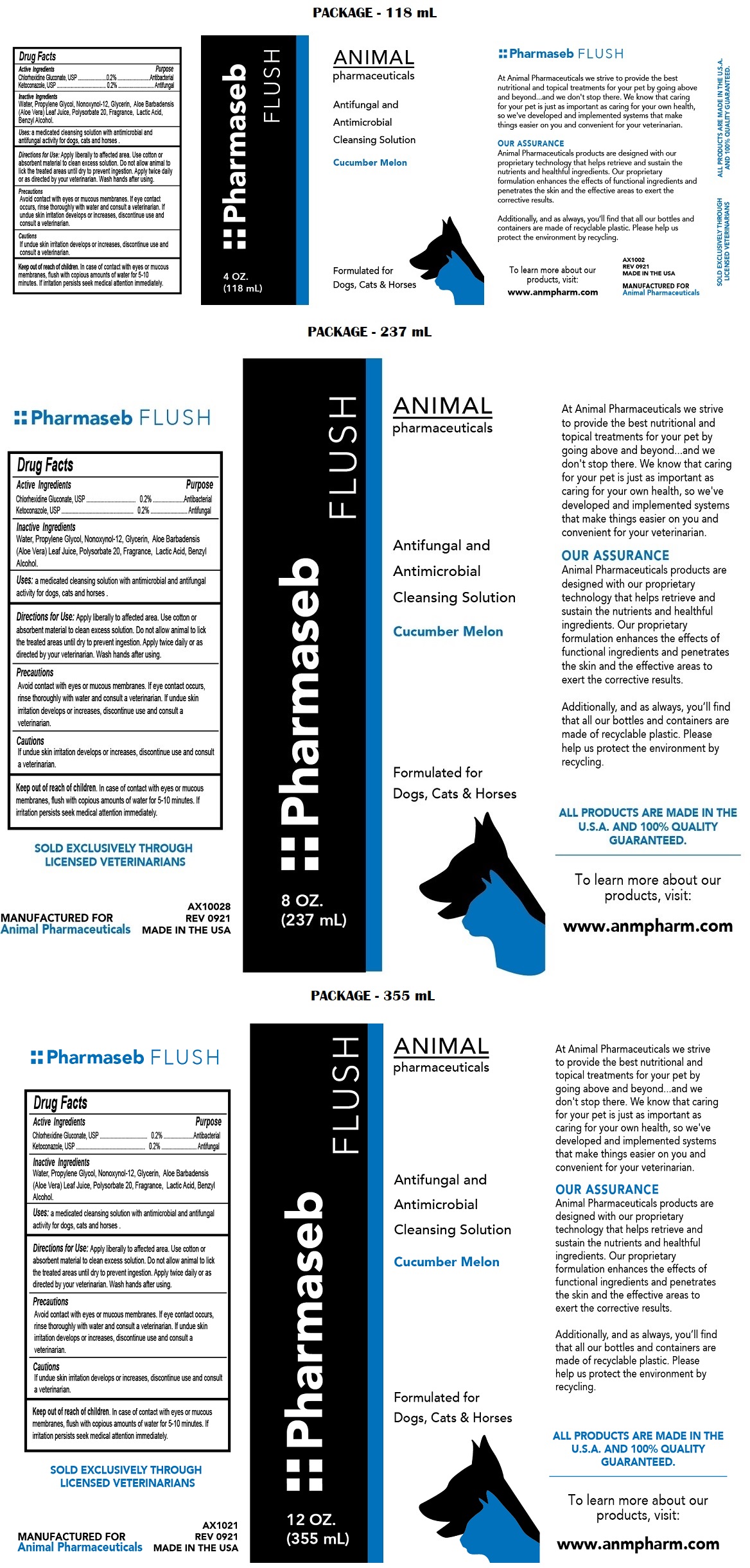 DRUG LABEL: Pharmaseb FLUSH
NDC: 68898-116 | Form: SOLUTION
Manufacturer: Animal Pharmaceuticals
Category: animal | Type: OTC ANIMAL DRUG LABEL
Date: 20221121

ACTIVE INGREDIENTS: CHLORHEXIDINE GLUCONATE 0.2 g/100 mL; KETOCONAZOLE 0.2 g/100 mL
INACTIVE INGREDIENTS: WATER; PROPYLENE GLYCOL; NONOXYNOL-12; GLYCERIN; ALOE VERA LEAF; POLYSORBATE 20; LACTIC ACID, UNSPECIFIED FORM; BENZYL ALCOHOL

Pharmaseb FLUSH

Active Ingredients

Chlorhexidine Gluconate, USP 0.2%

Ketoconazole, USP 0.2%

Purpose

Antibacterial

Antifungal

Inactive Ingredients

Water, Propylene Glycol, Nonoxynol-12, Glycerin, Aloe Barbadensis (Aloe Vera) Leaf Juice, Polysorbate 20, Fragrance, Lactic Acid, Benzyl Alcohol.

Uses:

a medicated cleansing solution with antimicrobial and antifungal activity for dogs, cats and horses.

Directions for Use:

Apply liberally to affected area. Use cotton or absorbent material to clean excess solution. Do not allow animal to lick the treated areas until dry to prevent ingestion. Apply twice daily or as directed by your veterinarian. Wash hands after using.

Precautions

Avoid contact with eyes or mucous membranes. If eye contact occurs, rinse thoroughly with water and consult a veterinarian. If undue skin irritation develops or increases, discontinue use and consult a veterinarian.

Cautions

If undue skin irritation develops or increases, discontinue use and consult a veterinarian.

Keep out of reach of children. In case of contact with eyes or mucous membranes, flush with copious amounts of water for 5-10 minutes. If irritation persists seek medical attention immediately.

Antifungal and Antimicrobial Cleansing Solution

Cucumber Melon

Formulated for Dogs, Cats & Horses

At Animal Pharmaceuticals we strive to provide the best nutritional and topical treatments for your pet by going above and beyond....and we don't stop there. We know that caring for your pet is just as important as caring for your own health, so we've developed and implemented systems that make things easier on you and convenient for your veterinarian.

OUR ASSURANCE
Animal Pharmaceuticals products are designed with our proprietary technology that helps retrieve and sustain the nutrients and healthful ingredients. Our proprietary formulation enhances the effects of functional ingredients and penetrates the skin and the effective areas to exert the corrective results.

Additionally, and as always, you'll find that all our bottles and containers are made of recyclable plastic. Please help us protect the environment by recycling.

ALL PRODUCTS ARE MADE IN THE U.S.A. AND 100% QUALITY GUARANTEED.

To learn more about our products, visit:

www.anmpharm.com

SOLD EXCLUSIVELY THROUGH LICENSED VETERINARIANS

MANUFACTURED FOR
Animal Pharmaceuticals

MADE IN THE USA